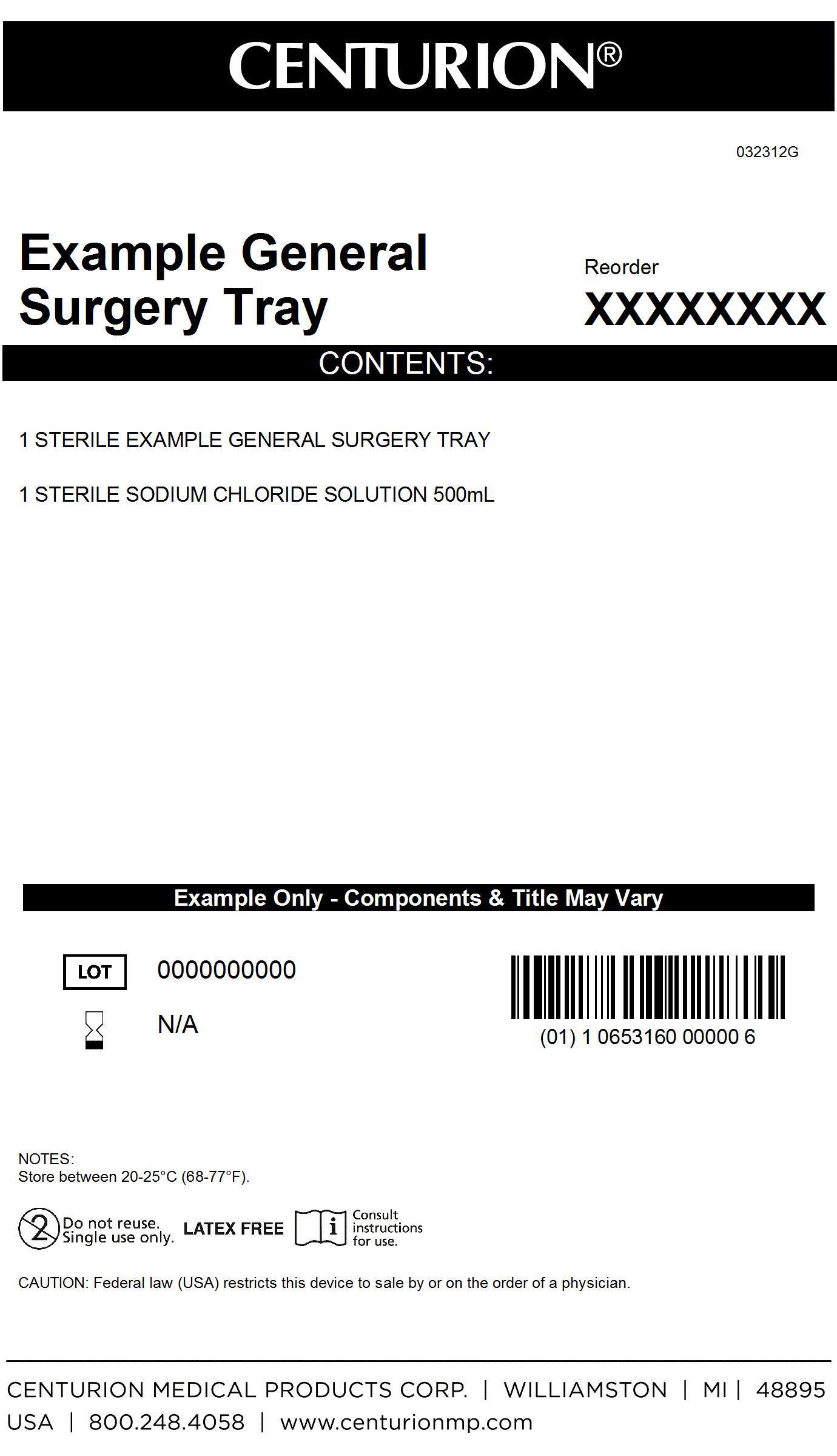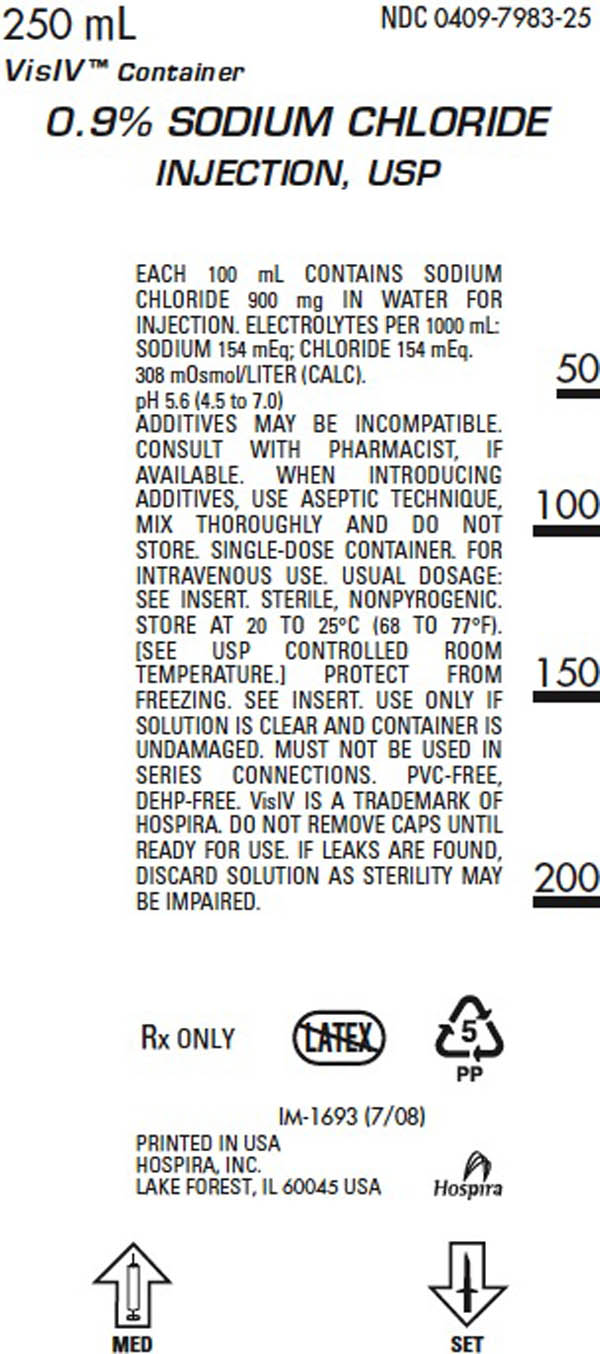 DRUG LABEL: General Surgery Kit
NDC: 24840-1535 | Form: KIT | Route: INTRAVENOUS
Manufacturer: Centurion Medical Products
Category: other | Type: MEDICAL DEVICE
Date: 20120927

ACTIVE INGREDIENTS: SODIUM CHLORIDE 900 mg/100 mL
INACTIVE INGREDIENTS: WATER

General Surgery Kit

DESCRIPTION

0.9% Sodium Chloride Injection, USP is sterile and nonpyrogenic. It is a parenteral solution containing sodium chloride in water for injection intended for intravenous administration. Each 100 ml of 0.9% sodium chloride injection, USP contains 900 mg sodium chloride in water for injection. The pH is 5.6 (4.5 to 7.0). This solution contains no bacteriostat, antimicrobial agent or added buffer and is intended only as a single-dose injection. When smaller doses are required, the unused portion should be discarded. 0.9% Sodium Chloride is a parenteral fluid and electolyte replenisher and is a white crystalline powder freely soluable in water.

PACKAGE LABEL

MM